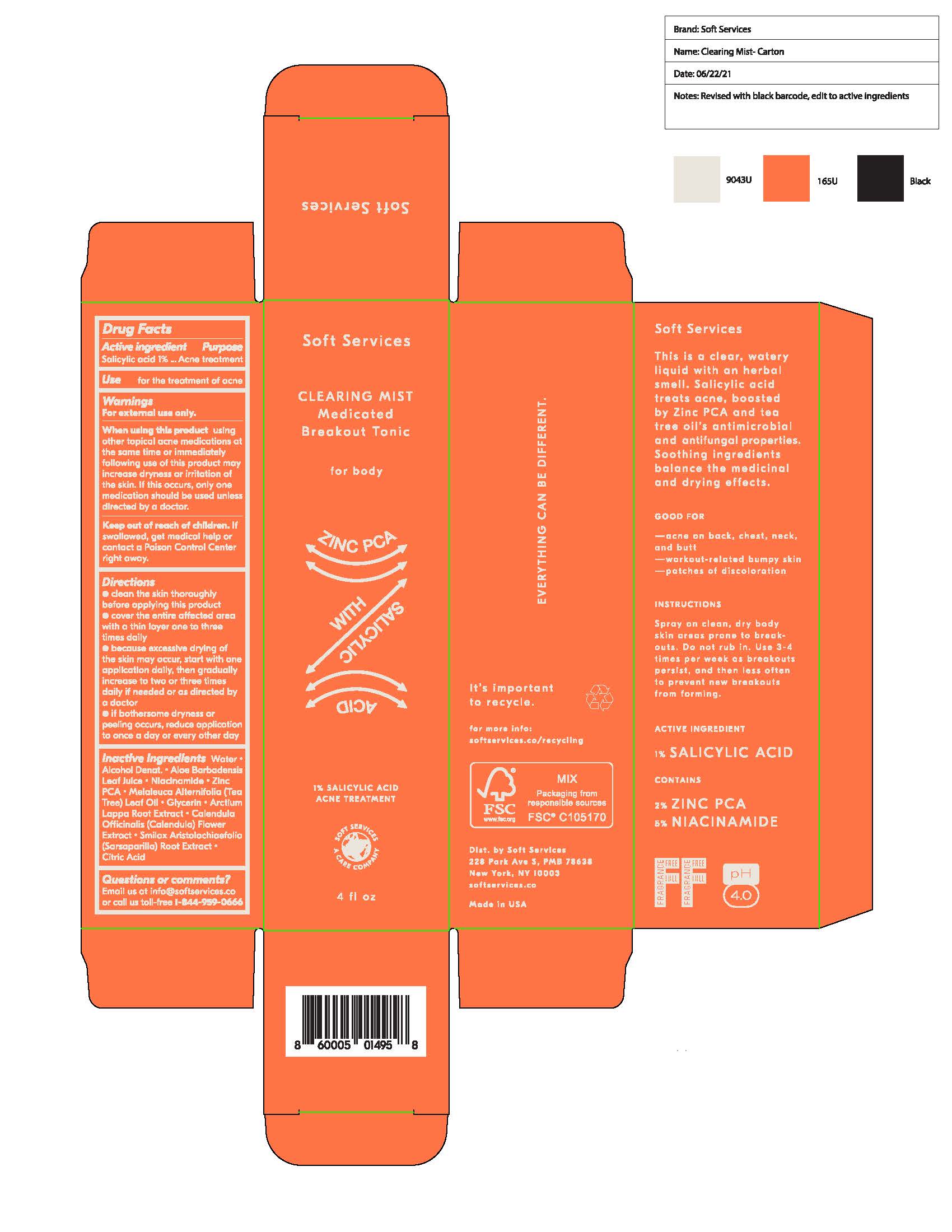 DRUG LABEL: Soft Services CLEARING Mist Breakout Tonic
NDC: 82030-010 | Form: LIQUID
Manufacturer: A TO Z INTERNATIONAL CORPORATION
Category: otc | Type: HUMAN OTC DRUG LABEL
Date: 20210630

ACTIVE INGREDIENTS: SALICYLIC ACID 1 g/100 g
INACTIVE INGREDIENTS: WATER; ALCOHOL; ALOE VERA LEAF; NIACINAMIDE; ZINC; MELALEUCA ALTERNIFOLIA LEAF; GLYCERIN; ARCTIUM LAPPA ROOT; CALENDULA OFFICINALIS FLOWER; SMILAX ARISTOLOCHIIFOLIA ROOT; CITRIC ACID MONOHYDRATE

DRUG FACTS

Active Ingredients

Salicylic Acid 1%

Purpose

Acne Treatment

Uses

• for the treatment of acne

Warnings

For external use only
Using other topical acne medications at the same time or immediately following use of this
product may increase dryness or irritation of the skin. If this occurs, only one medication should
be used unless directed by a doctor.

Keep out of reach of children. If swallowed, get medical help or contact a Poison Control Center right away.

Directions

• clean the skin thoroughly before applying this product • cover the entire
affected area with a thin layer one to three times daily • because excessive drying of the
skin may occur, start with one application daily, then gradually increase to two or three times
daily if needed or as directed by a doctor • if bothersome dryness or peeling occurs, reduce
application to once a day or every other day.

Inactive Ingredients

Water, Alcohol Deant., Aloe Barbadensis Leaf Juice, Niacinamide, Zinc PCA, Melaleuca Alternifolia Leaf Oil, Glycerin, Arctium Lappa Root Extract, Calendula Officinalis Flower Extract, Smilax Aristolochiaefolia Root Extrac, Citric Acid

Questions or comments?

Email us at info@softservices.co or call us toll-free 1-844-959-0666